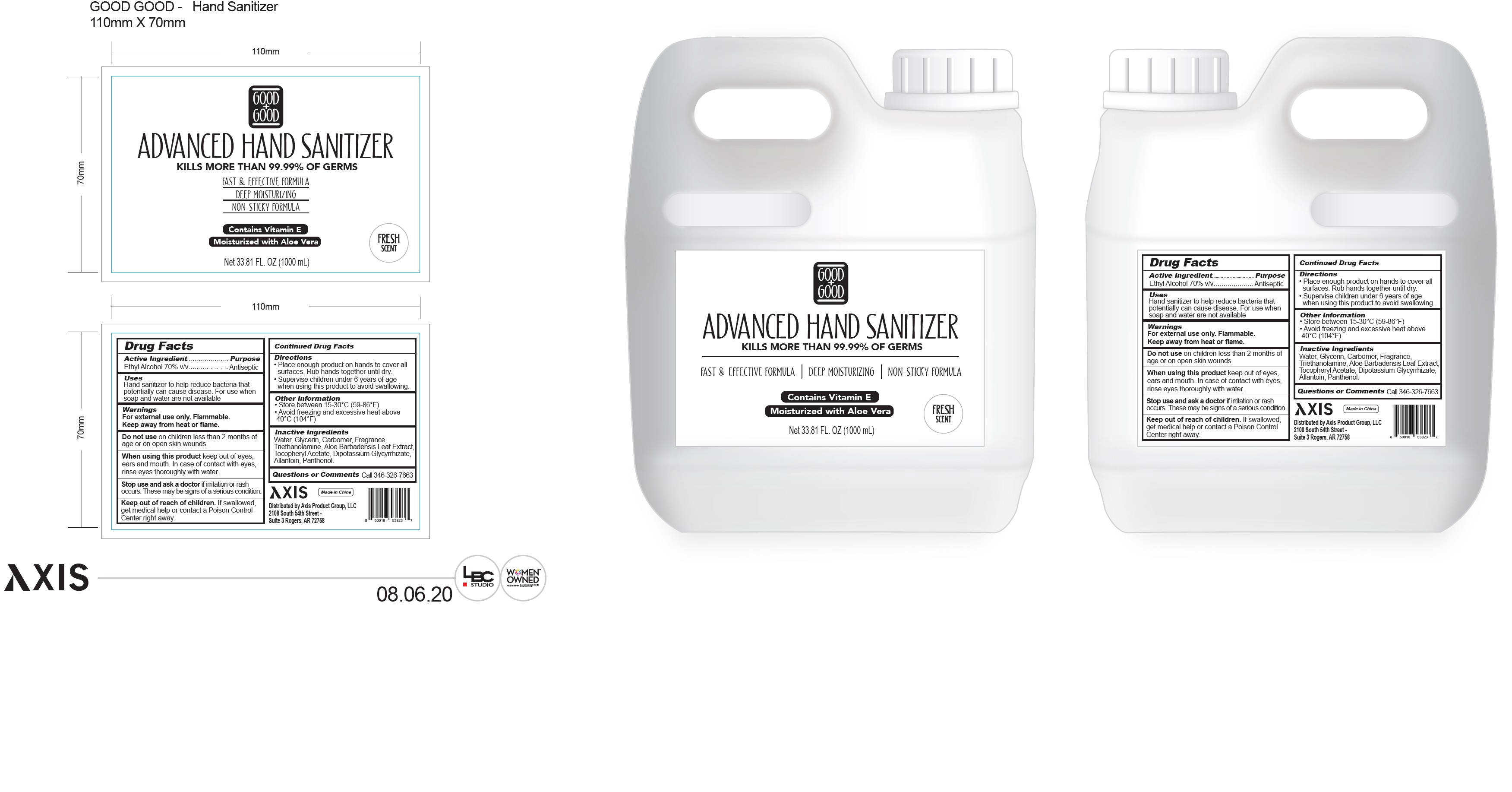 DRUG LABEL: Good Good Advanced Hand Sanitizer
NDC: 79541-101 | Form: GEL
Manufacturer: Axis Product Group, LLC
Category: otc | Type: HUMAN OTC DRUG LABEL
Date: 20200930

ACTIVE INGREDIENTS: ALCOHOL 0.7 mL/1 mL
INACTIVE INGREDIENTS: WATER; GLYCERIN; CARBOMER HOMOPOLYMER, UNSPECIFIED TYPE; TROLAMINE; ALOE VERA LEAF; .ALPHA.-TOCOPHEROL ACETATE; GLYCYRRHIZINATE DIPOTASSIUM; ALLANTOIN; PANTHENOL

Good+Good Advanced Hand Sanitizer

Active Ingredient

Ethyl Alcohol 70% v/v

Purpose

Antiseptic

Uses

Hand sanitizer to help reduce bacterial that potentially can cause disease. For use when soap and water are not available.

Warnings

For external use only. Flammable. Keep away from heat or flame.

Do not use

on children less than 2 months of age or on open skin wounds.

When using this product

keep out of eyes, ears and mouth. In case of contact with eyes, rinse eyes thoroughly with water.

Stop use and ask a doctor

if irritation or rash occurs. These may be signs of a serious condition.

Keep out of reach of children.

If swallowed, get medical help or contact a Poison Control Center right away.

Directions

- Place enough product on hands to cover all surfaces. Rub hands together until dry.
- Supervise children under 6 years of age when using this product to avoid swallowing.

Other Information

- Store between 15-30°C (59-86°F)
- Avoid freezing and excessive heat above 40°C (104°F)

Inactive Ingredients

Water, Glycerin, Carbomer, Fragrance, Triethanolamine, Aloe Barbadensis Leaf Extract, Tocopheryl Acetate, Dipotassium Glycyrrhizate, Allantoin, Panthenol.

Questions or Comments

Call 346-326-7663